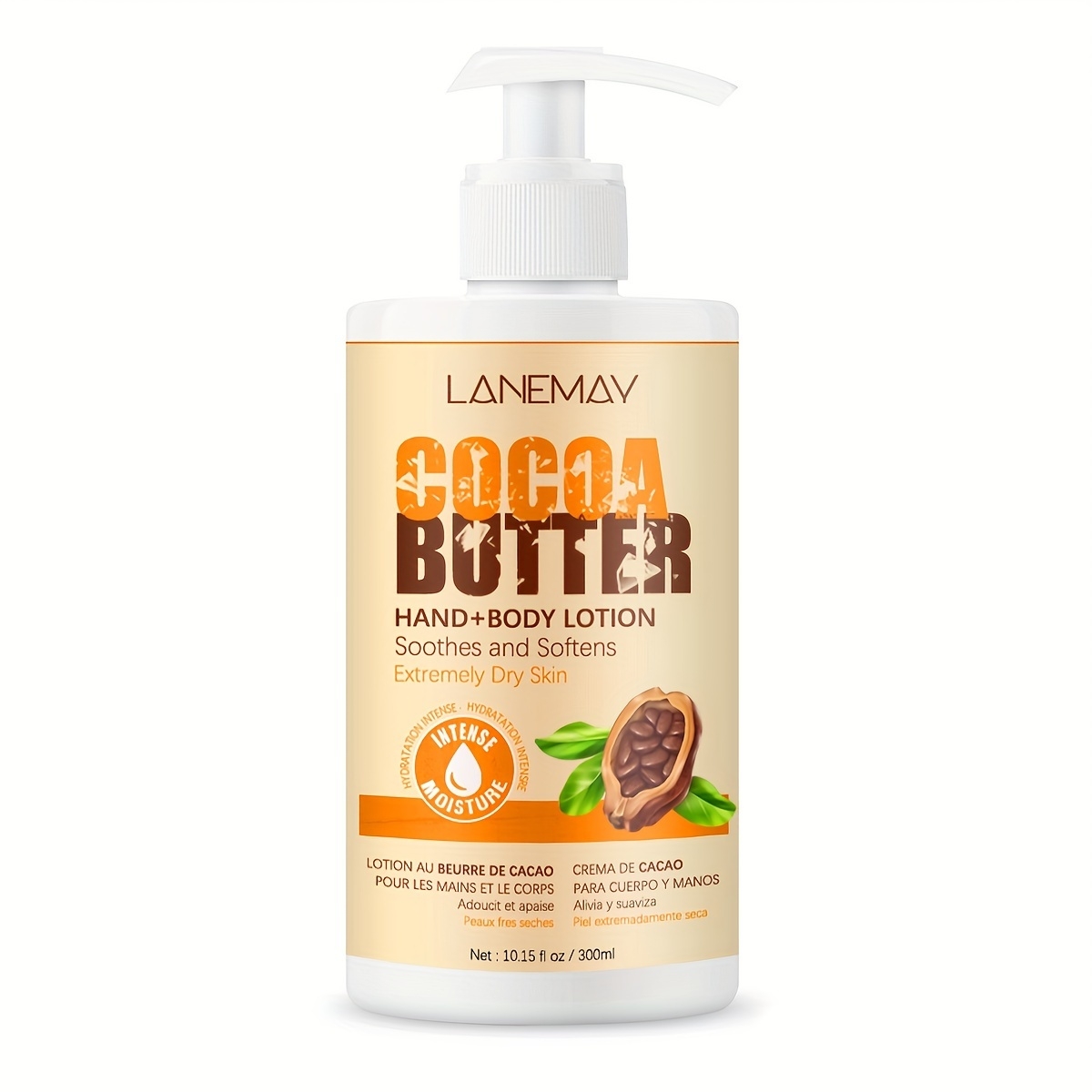 DRUG LABEL: cocoa butter hand bodylotion
NDC: 84025-218 | Form: CREAM
Manufacturer: Guangzhou Yanxi Biotechnology Co., Ltd
Category: otc | Type: HUMAN OTC DRUG LABEL
Date: 20241018

ACTIVE INGREDIENTS: GLYCERIN 12 mg/300 mL; MINERAL OIL 15 mg/300 mL
INACTIVE INGREDIENTS: WATER

DOSAGE AND ADMINISTRATION

After bathing, evenly apply the product to the body and gently massage until absorbed.

WARNINGS

Keep out of children

INACTIVE INGREDIENT

Aqua

INDICATIONS AND USAGE

For daily skin care

Keep out of children

PURPOSE

Skin moisturizing